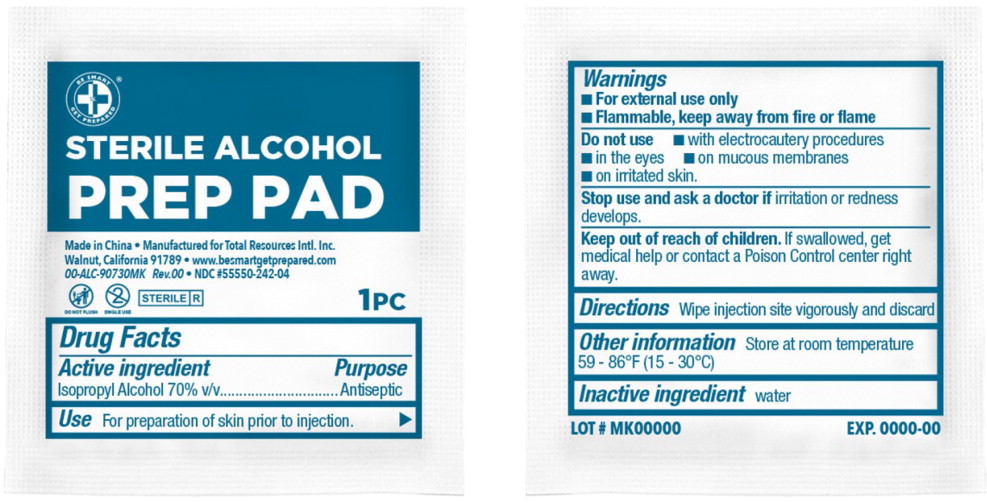 DRUG LABEL: Be Smart Get Prepared Alcohol Prep Pad
NDC: 55550-242 | Form: CLOTH
Manufacturer: Total Resources International, Inc
Category: otc | Type: HUMAN OTC DRUG LABEL
Date: 20250414

ACTIVE INGREDIENTS: ISOPROPYL ALCOHOL 0.7 mL/1 mL
INACTIVE INGREDIENTS: WATER

DRUG FACTS

Active Ingredient

- Alcohol 70% v/v………………………………………………………

Purpose

- Antiseptic

USE

- For preparation of skin prior to injection

WARNINGS

- For external use only.
- Flammable, keep away from fire or flame

- Do not use
  - With electrocautery procedures
  - In the eyes
  - On mucous membranes
  - On irritated skin

- Stop use and ask a doctor if irritation or redness develops

- Keep out of reach of children. If swallowed, get medical help or contact a Poison Control Center right away

DIRECTIONS

- Wipe injection site vigorously and discard

OTHER INFORMATION

- Store at room temperature

INACTIVE INGREDIENT

- Purified water

Principal Display Panel

BE SMART

GET PREPARED®

STERILE ALCOHOL PREP PAD

1 PC

Single Use

Do Not Flush

Sterile

Made in China

Manufactured for Total Resources Intl. Inc
Walnut, California 91789

www.besmartgetprepared.com • 00-ALC-90730MK Rev. 00

NDC 55550-242-04